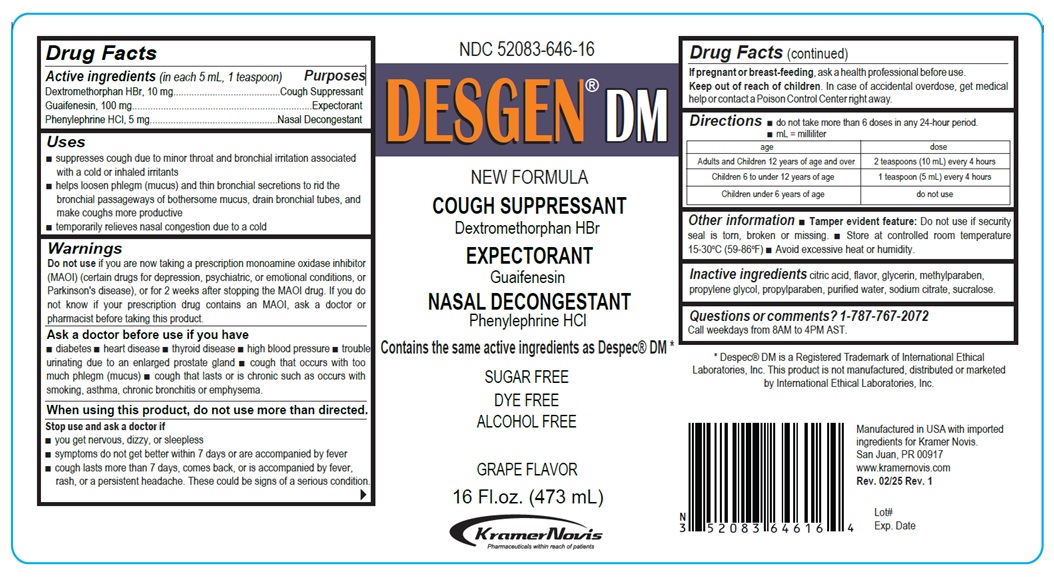 DRUG LABEL: DESGEN DM
NDC: 52083-646 | Form: SOLUTION
Manufacturer: Kramer Novis
Category: otc | Type: HUMAN OTC DRUG LABEL
Date: 20251112

ACTIVE INGREDIENTS: DEXTROMETHORPHAN HYDROBROMIDE 10 mg/5 mL; GUAIFENESIN 100 mg/5 mL; PHENYLEPHRINE HYDROCHLORIDE 5 mg/5 mL
INACTIVE INGREDIENTS: CITRIC ACID MONOHYDRATE; GLYCERIN; METHYLPARABEN; PROPYLENE GLYCOL; PROPYLPARABEN; WATER; SODIUM CITRATE, UNSPECIFIED FORM; SUCRALOSE

DESGEN® DM

Active ingredients (in each 5 mL, 1 teaspoon)

Dextromethorphan HBr, 10 mg

Guaifenesin, 100 mg

Phenylephrine HCl, 5 mg

Purposes

Cough Suppressant

Expectorant

Nasal Decongestant

Uses

• suppresses cough due to minor throat and bronchial irritation associated with a cold or inhaled irritants
• helps loosen phlegm (mucus) and thin bronchial secretions to rid the bronchial passageways of bothersome mucus, drain bronchial tubes, and make coughs more productive
• temporarily relieves nasal congestion due to a cold

Warnings

Do not use if you are now taking a prescription monoamine oxidase inhibitor (MAOI) (certain drugs for depression, psychiatric, or emotional conditions, or Parkinson’s disease), or for 2 weeks after stopping the MAOI drug. If you do not know if your prescription drug contains an MAOI, ask a doctor or pharmacist before taking this product.

Ask a doctor before use if you have
• diabetes • heart disease • thyroid disease • high blood pressure • trouble urinating due to an enlarged prostate gland • cough that occurs with too much phlegm (mucus) • cough that lasts or is chronic such as occurs with smoking, asthma, chronic bronchitis or emphysema.

When using this product do not use more than directed.

Stop use and ask a doctor if
• you get nervous, dizzy, or sleepless
• symptoms do not get better within 7 days or are accompanied by fever
• coughs lasts more than 7 days, comes back, or is accompanied by fever, rash, or a persistent headache. These could be signs of a serious condition.

If pregnant or breast-feeding, ask a health professional before use.

Keep out of reach of children. In case of accidental overdose, get medical help or contact a Poison Control Center right away.

Directions

• do not take more than 6 doses in any 24-hour period.
• mL = milliliter

age | dose
Adults and Children 12 years of age and over | 2 teaspoons (10 mL) every 4 hours
Children 6 to under 12 years of age | 1 teaspoon (5 mL) every 4 hours
Children under 6 years of age | do not use

Other information

• Tamper evident feature: Do not use if security seal is torn, broken or missing. • Store at controlled room temperature 15-30°C (59-86°F) • Avoid excessive heat or humidity.

Inactive ingredients

citric acid, flavor, glycerin, methylparaben, propylene glycol, propylparaben, purified water, sodium citrate, sucralose.

Questions or comments?

1-787-767-2072
Call weekdays from 8AM to 4PM AST.

NEW FORMULA

COUGH SUPPRESSANT
Dextromethorphan HBr

EXPECTORANT
Guaifenesin

NASAL DECONGESTANT
Phenylephrine HCl

Contains the same active ingredients as Despec® DM *

SUGAR FREE

DYE FREE

ALCOHOL FREE

GRAPE FLAVOR

Kramer Novis
Pharmaceuticals within reach of patients

* Despec® DM is a Registered Trademark of International Ethical Laboratories, Inc. This product is not manufactured, distributed or marketed by International Ethical Laboratories, Inc.

Manufactured in USA with imported ingredients for Kramer Novis.
San Juan, PR 00917
www.kramernovis.com